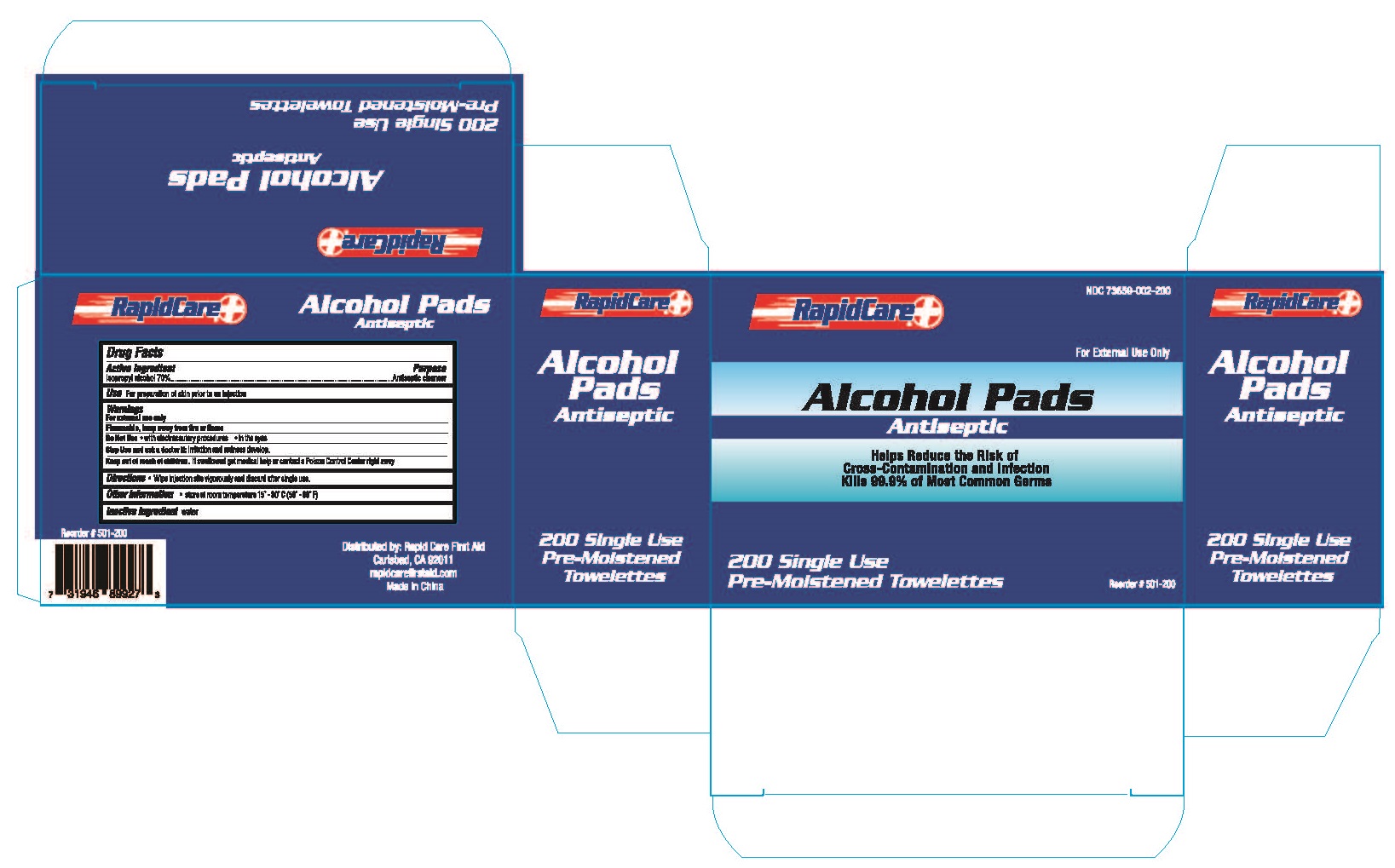 DRUG LABEL: Alcohol Pads
NDC: 73659-002 | Form: SWAB
Manufacturer: Rapid Care, Inc
Category: otc | Type: HUMAN OTC DRUG LABEL
Date: 20211014

ACTIVE INGREDIENTS: ISOPROPYL ALCOHOL 0.7 mL/1 1
INACTIVE INGREDIENTS: WATER

Rapid Care - Alcohol Wipes 200pcs

Active Ingredients

Isopropyl Alcohol, 70%

Purpose

Antiseptic cleanser

Use

For preparation of skin prior to an injection

Warnings

For external use only

Do Not Use

- with electrocautery procedures
- In or near the eyes, if contact occurs, flush eyse with water.

Stop Use and ask a doctor:

- irration and redness develop.

Keep out of reach of children.

If swallowed get medical help or contact a Poison Control right away.

Directions

- wipe injection site vigorously and discard.

Other Information

stor at room temperaturel15°-30° C (59°-86° F)

Inactive ingredient

purified water